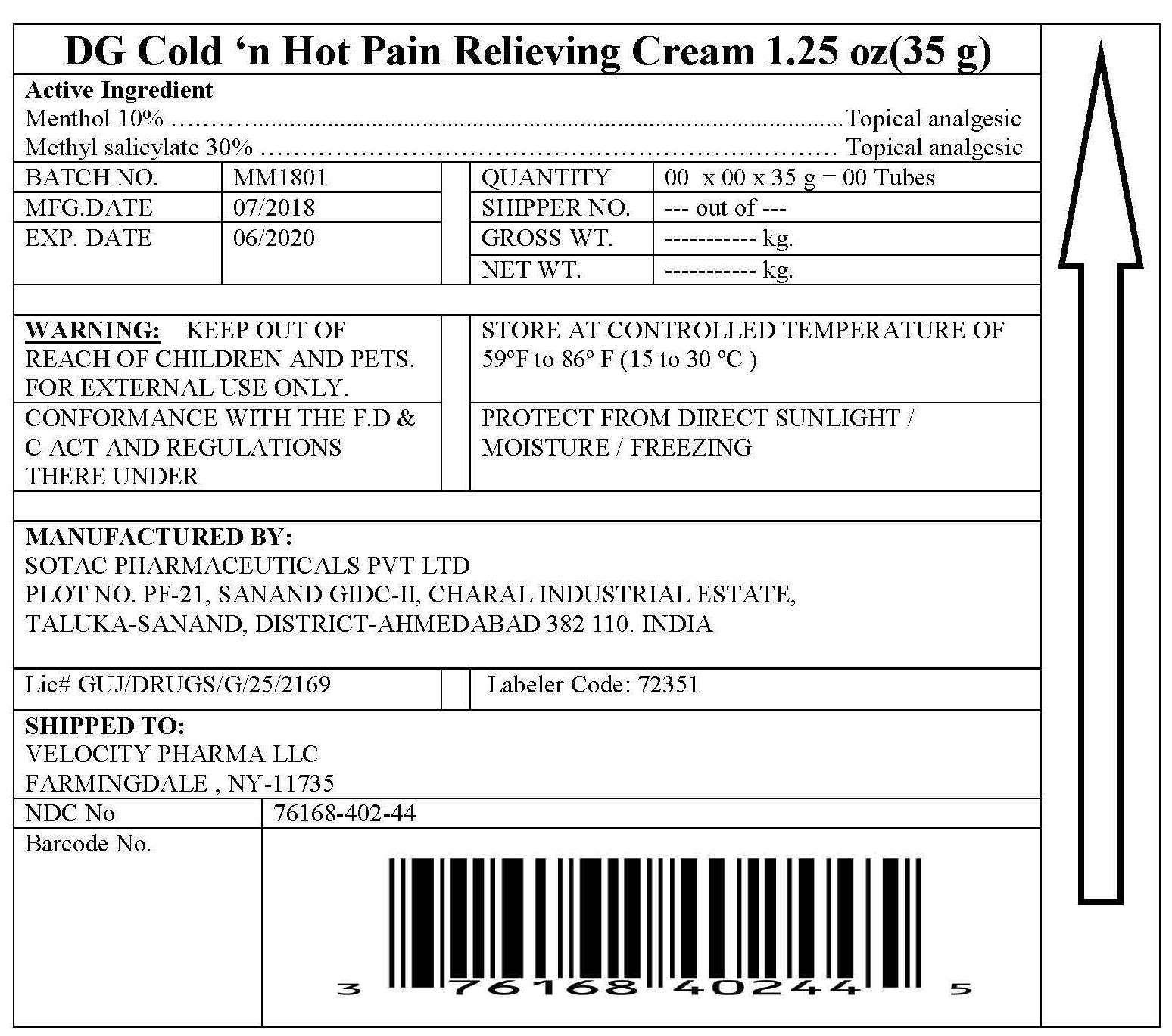 DRUG LABEL: Cold and Heat Pain Relieving Cream
NDC: 72351-010 | Form: CREAM
Manufacturer: SOTAC PHARMACEUTICALS PRIVATE LIMITED
Category: otc | Type: HUMAN OTC DRUG LABEL
Date: 20180809

ACTIVE INGREDIENTS: MENTHOL 10 g/100 g; METHYL SALICYLATE 30 g/100 g
INACTIVE INGREDIENTS: CETYL ESTERS WAX; OLETH-3 PHOSPHATE; STEARIC ACID; WATER; TROLAMINE

Cold and Heat Pain Relieving Cream

Drug Facts

Active ingredient

Menthol 10%

Methyl salicylate 30%

Purpose

Topical analgesic

Uses

temporarily relieves minor pain associated with:

- arthritis
- simple backache
- muscle strains
- sprains
- bruises
- cramps

Warnings

For external use only

SEE INSIDE LABEL FOR COMPLETE DRUG FACTS

Allergy Alert: If prone to allergic reaction from aspirin or salicylates, consult a doctor before use.

When using this product

- use only as directed
- do not bandage tightly or use with a heating pad
- avoid contact with eyes or mucous membranes
- do not apply to wounds or damaged, broken or irritated skin

Stop use and ask a doctor if

- condition worsens
- redness is present
- irritation develops
- symptoms persist for more than 7 days or clear up and occur again within a few days

If pregnant or breast-feeding,

ask a health care professional before use.

Keep out of reach of children.

If swallowed, get medical help or contact a Poison Control Center right away.

Directions

adults and children over 12 years:

- apply generously to affected area
- massage into painful area until thoroughly absorbed into skin
- repeat as necessary, but not more than 4 times daily

children 12 years or younger: ask a doctor

Inactive ingredients

ceresin, cyclomethicone, hydrogenated castor oil, microcrystalline wax, paraffin, PEG-150 distearate, propylene glycol, stearic acid, stearyl alcohol (245-111)